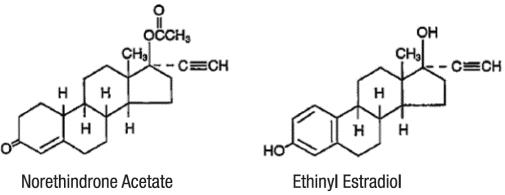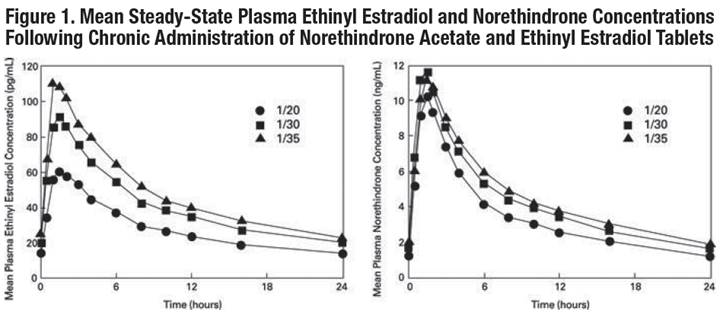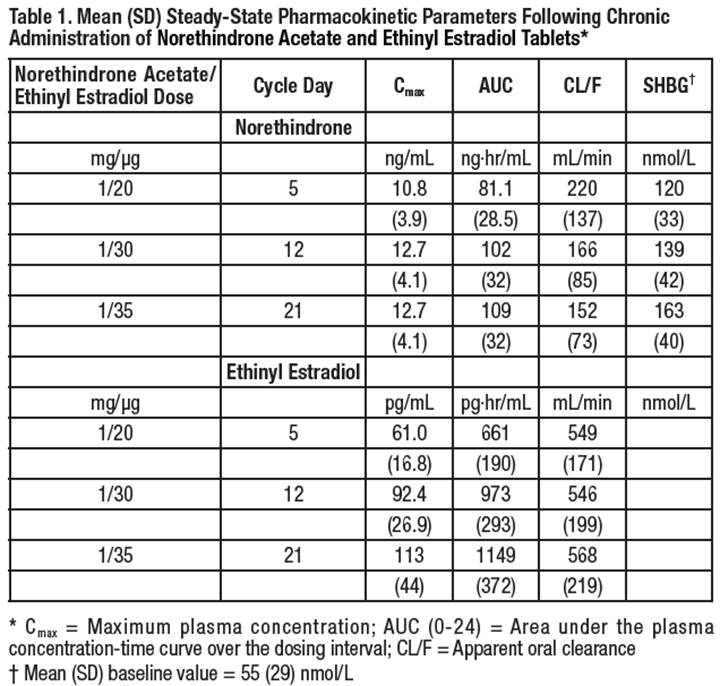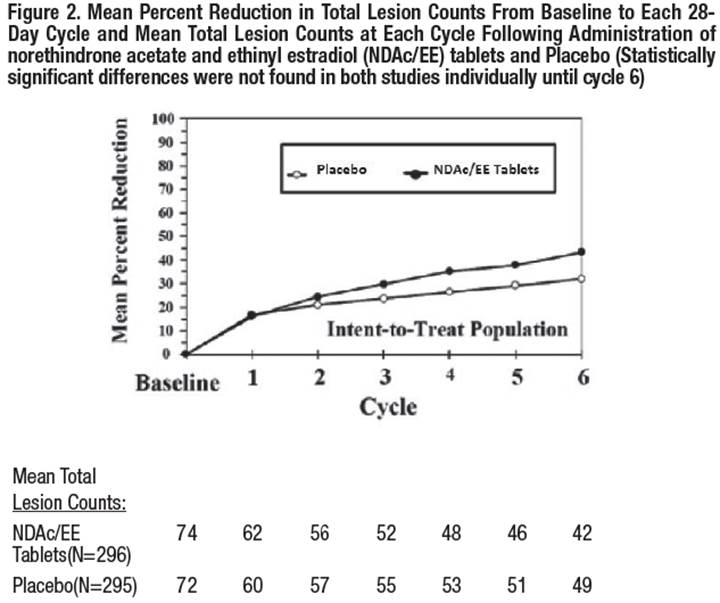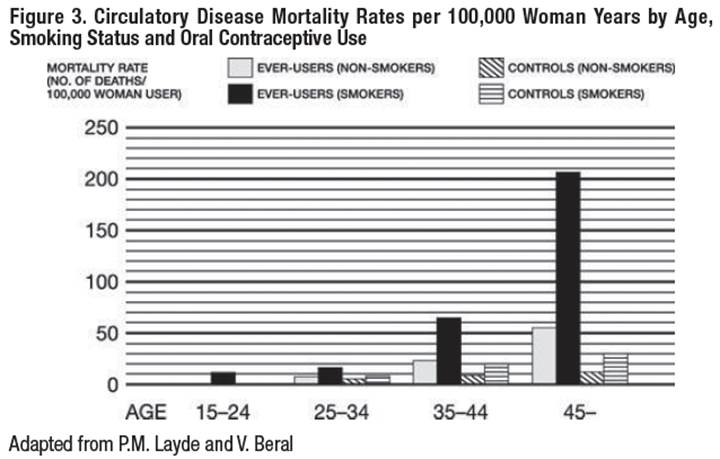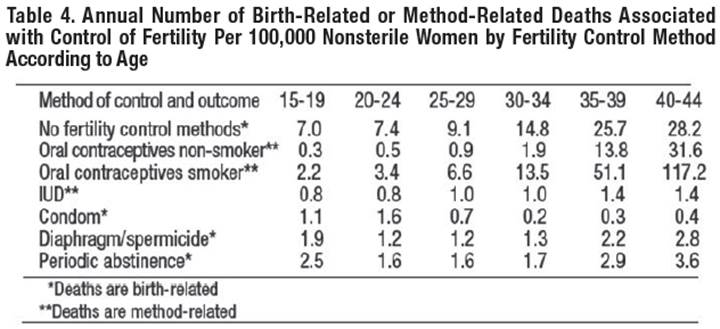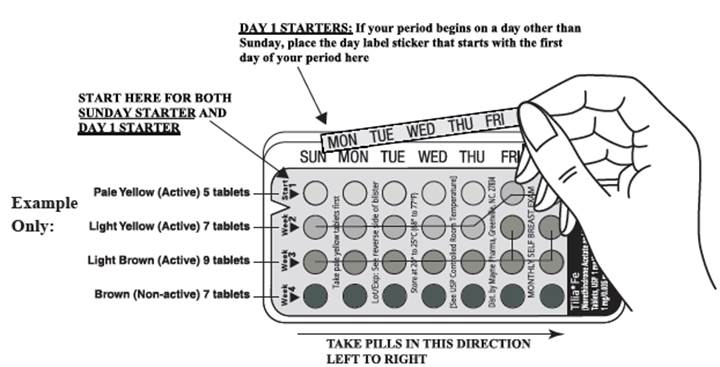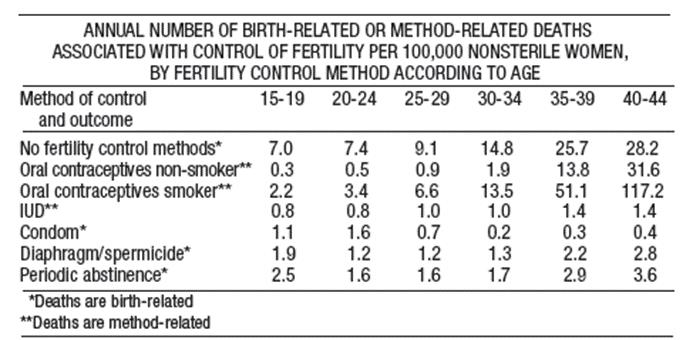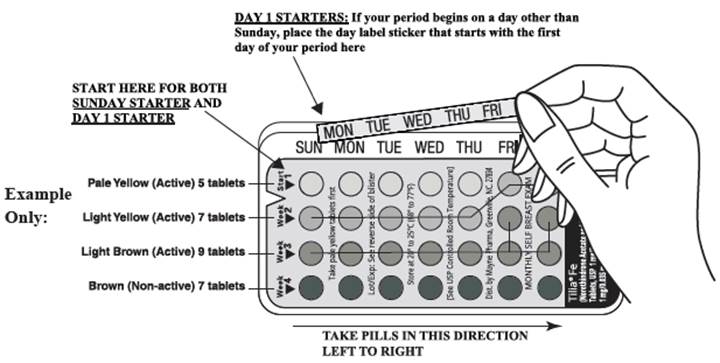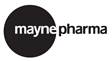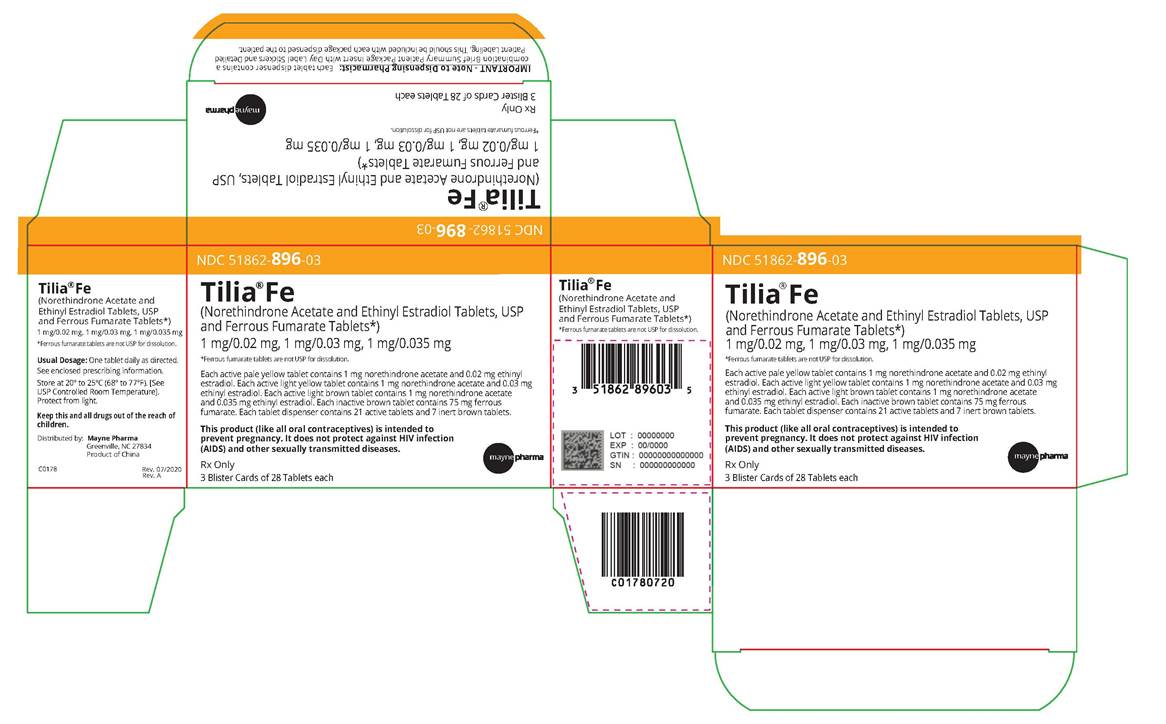 DRUG LABEL: Tilia Fe 								
NDC: 51862-896 | Form: KIT | Route: ORAL
Manufacturer: Mayne Pharma Inc.
Category: prescription | Type: HUMAN PRESCRIPTION DRUG LABEL
Date: 20250908

ACTIVE INGREDIENTS: NORETHINDRONE ACETATE 1 mg/1 1; ETHINYL ESTRADIOL 0.02 mg/1 1; NORETHINDRONE ACETATE 1 mg/1 1; ETHINYL ESTRADIOL 0.03 mg/1 1; NORETHINDRONE ACETATE 1 mg/1 1; ETHINYL ESTRADIOL 0.035 mg/1 1
INACTIVE INGREDIENTS: ETHYLCELLULOSE, UNSPECIFIED; HYPROMELLOSE, UNSPECIFIED; LACTOSE MONOHYDRATE; STARCH, CORN; MAGNESIUM STEARATE; POLYVINYL ALCOHOL, UNSPECIFIED; TITANIUM DIOXIDE; TALC; POLYETHYLENE GLYCOL 3350; SOYBEAN LECITHIN; D&C YELLOW NO. 10 ALUMINUM LAKE; FD&C BLUE NO. 2 ALUMINUM LAKE; FD&C YELLOW NO. 6; ETHYLCELLULOSE, UNSPECIFIED; HYPROMELLOSE, UNSPECIFIED; LACTOSE MONOHYDRATE; STARCH, CORN; MAGNESIUM STEARATE; POLYVINYL ALCOHOL, UNSPECIFIED; TITANIUM DIOXIDE; TALC; POLYETHYLENE GLYCOL 3350; SOYBEAN LECITHIN; D&C YELLOW NO. 10 ALUMINUM LAKE; FD&C BLUE NO. 2 ALUMINUM LAKE; FD&C YELLOW NO. 6; FERRIC OXIDE YELLOW; ETHYLCELLULOSE, UNSPECIFIED; HYPROMELLOSE, UNSPECIFIED; LACTOSE MONOHYDRATE; STARCH, CORN; MAGNESIUM STEARATE; POLYVINYL ALCOHOL, UNSPECIFIED; TITANIUM DIOXIDE; TALC; POLYETHYLENE GLYCOL 3350; SOYBEAN LECITHIN; FERRIC OXIDE YELLOW; FERRIC OXIDE RED; FERROSOFERRIC OXIDE; MICROCRYSTALLINE CELLULOSE; FERROUS FUMARATE; MAGNESIUM STEARATE; HYDROXYPROPYL CELLULOSE, UNSPECIFIED; CROSPOVIDONE, UNSPECIFIED; POLYVINYL ALCOHOL, UNSPECIFIED; FERRIC OXIDE YELLOW; FERRIC OXIDE RED; FERROSOFERRIC OXIDE; TALC; POLYETHYLENE GLYCOL 3350; SOYBEAN LECITHIN

Tilia® Fe(Norethindrone Acetate and Ethinyl Estradiol Tablets, USP and Ferrous Fumarate Tablets*)
1 mg/0.02 mg, 1 mg/0.03 mg, 1 mg/0.035 mg
*Ferrous fumarate tablets are not USP for dissolution.

Tilia Fe

(Each pale yellow tablet contains 1 mg norethindrone acetate and 20 mcg ethinyl estradiol; each light yellow tablet contains 1 mg norethindrone acetate and 30 mcg ethinyl estradiol; each light brown tablet contains 1 mg norethindrone acetate and 35 mcg ethinyl estradiol; each brown tablet contains 75 mg ferrous fumarate.)

Patients should be counseled that this product does not protect against HIV infection (AIDS) and other sexually transmitted diseases.

DESCRIPTION

Tilia Fe is a graduated estrophasic oral contraceptive providing estrogen in a graduated sequence over a 21-day period with a constant dose of progestogen.

Tilia Fe provides for a continuous dosage regimen consisting of 21 oral contraceptive tablets and seven ferrous fumarate tablets. The ferrous fumarate tablets are present to facilitate ease of drug administration via a 28-day regimen, are non-hormonal, and do not serve any therapeutic purpose.

Each pale yellow tablet contains 1 mg norethindrone acetate [(17 alpha)-17-(acetyloxy)-19-norpregna-4-en-20-yn-3-one] and 20 mcg ethinyl estradiol [(17 alpha)-19-norpregna-1,3,5(10)-trien-20-yne-3,17-diol]; each light yellow tablet contains 1 mg norethindrone acetate and 30 mcg ethinyl estradiol; and each light brown tablet contains 1mg norethindrone acetate and 35mcg ethinyl estradiol.

Each pale yellow tablet contains 1 mg norethindrone acetate and 20 mcg ethinyl estradiol.Each pale yellow tablet contains the following inactive ingredients: Ethyl Cellulose, Hypromellose, Lactose Monohydrate, Pregelatinized Starch, Magnesium Stearate, Polyvinyl Alcohol, Titanium Dioxide ,Talc, Macrogol/Polyethylene Glycol, Lecithin (Soya),D&C Yellow #10 Aluminum Lake, FD&C Blue #2 Aluminum Lake, FD&C Yellow #6 Aluminum Lake.

Each light yellow tablet contains 1 mg norethindrone acetate and 30 mcg ethinyl estradiol. Each light yellow tablet contains the following inactive ingredients: Ethyl Cellulose, Hypromellose, Lactose Monohydrate, Pregelatinized Starch, Magnesium Stearate, Polyvinyl Alcohol, Titanium Dioxide , Talc , Macrogol/Polyethylene Glycol, Lecithin (Soya), D&C Yellow #10 Aluminum Lake, Iron Oxide Yellow, FD&C Yellow #6 Aluminum Lake, FD&C Blue #2 Aluminum Lake.

Each light brown tablet contains 1 mg norethindrone acetate and 35 mcg ethinyl estradiol. Each light brown tablet contains the following inactive ingredients: Ethyl Cellulose, Hypromellose, Lactose Monohydrate, Pregelatinized Starch, Magnesium Stearate, Polyvinyl Alcohol, Titanium Dioxide,Talc , Macrogol/Polyethylene Glycol, Lecithin (Soya), Iron Oxide Yellow, Iron Oxide Red, Iron Oxide Black.

The structural formulas are as follows:

Each brown tablet contains: Ferrous Fumarate, Micro-crystalline Cellulose, Hydroxypropyl Cellulose, Crospovidone, Magnesium Stearate, Polyvinyl Alcohol, Iron Oxide Yellow, Talc, Polyethylene Glycol 3350, Iron Oxide Red, Lecithin (Soya), Iron Oxide Black.

Each Tilia Fe tablet dispenser contains five pale yellow tablets, seven light yellow tablets, nine light brown tablets, and seven brown tablets. These tablets are to be taken in the following order: one pale yellow tablet each day for five days, then one light yellow tablet each day for seven days, followed by one light brown tablet each day for nine days, and then one brown tablet each day for seven days.

CLINICAL PHARMACOLOGY

ORAL CONTRACEPTION

Combination oral contraceptives act by suppression of gonadotropins. Although the primary mechanism of this action is inhibition of ovulation, other alterations include changes in the cervical mucus (which increase the difficulty of sperm entry into the uterus) and the endometrium (which reduce the likelihood of implantation).

In vitro and animal studies have shown that norethindrone combines high progestational activity with low intrinsic androgenicity. In humans, norethindrone acetate in combination with ethinyl estradiol does not counteract estrogen-induced increases in sex hormone binding globulin (SHBG). Following multiple-dose administration of norethindrone acetate and ethinyl estradiol tablets, serum SHBG concentrations increase two- to three-fold and free testosterone concentrations decrease by 47% to 64%, indicating minimal androgenic activity.

ACNE

Acne is a skin condition with a multifactorial etiology, including androgen stimulation of sebum production. While the combination of norethindrone acetate and ethinyl estradiol increases sex hormone binding globulin (SHBG) and decreases free testosterone, the relationship between these changes and a decrease in the severity of facial acne in otherwise healthy women with this skin condition has not been established.

Pharmacokinetics

Absorption

Norethindrone acetate appears to be completely and rapidly deacetylated to norethindrone after oral administration, since the disposition of norethindrone acetate is indistinguishable from that of orally administered norethindrone. Norethindrone acetate and ethinyl estradiol are rapidly absorbed, with maximum plasma concentrations of norethindrone and ethinyl estradiol occurring 1 to 2 hours post-dose. Both are subject to first-pass metabolism after oral dosing, resulting in an absolute bioavailability of approximately 64% for norethindrone and 43% for ethinyl estradiol.

Administration of norethindrone acetate/ethinyl estradiol with a high fat meal decreases rate, but not extent,of ethinyl estradiol absorption. The extent of norethindrone absorption is increased by 27% following administration with food.

Plasma concentrations of norethindrone and ethinyl estradiol following chronic administration of norethindrone acetate and ethinyl estradiol tablets to 17 women are shown below (Figure 1). Mean steady-state concentrations of norethindrone for the 1/20, 1/30, and 1/35 tablet strengths increased as ethinyl estradiol dose increased over the 21-day dose regimen, due to dose-dependent effects of ethinyl estradiol on serum SHBG concentrations (Table 1).Mean steady-state plasma concentrations of ethinyl estradiol for the 1/20, 1/30, and 1/35 tablet strengths were proportional to ethinyl estradiol dose (Table 1).

No age-related differences were seen in plasma concentrations of ethinyl estradiol and norethindrone following administration of norethindrone acetate and ethinyl estradiol tablets to 119 postmenarchal women ages 15 to 48 years.

Distribution

Volume of distribution of norethindrone and ethinyl estradiol ranges from 2 to 4 L/kg. Plasma protein binding of both steroids is extensive (>95%); norethindrone binds to both albumin and sex hormone binding globulin, whereas ethinyl estradiol binds only to albumin. Although ethinyl estradiol does not bind to SHBG, it induces SHBG synthesis. Norethindrone acetate and ethinyl estradiol tablets increase serum SHBG concentrations two- to three-fold (Table 1).

Metabolism

Norethindrone undergoes extensive biotransformation, primarily via reduction, followed by sulfate and glucuronide conjugation. The majority of metabolites in the circulation are sulfates, with glucuronides accounting for most of the urinary metabolites. A small amount of norethindrone acetate is metabolically converted to ethinyl estradiol. Ethinyl estradiol is also extensively metabolized, both by oxidation and by conjugation with sulfate and glucuronide. Sulfates are the major circulating conjugates of ethinyl estradiol and glucuronides predominate in urine. The primary oxidative metabolite is 2-hydroxy ethinyl estradiol, formed by the CYP3A4 isoform of cytochrome P450. Part of the first-pass metabolism of ethinyl estradiol is believed to occur in gastrointestinal mucosa. Ethinyl estradiol may undergo enterohepatic circulation.

Excretion

Norethindrone and ethinyl estradiol are excreted in both urine and feces, primarily as metabolites. Plasma clearance values for norethindrone and ethinyl estradiol are similar (approximately 0.4 L/hr/kg). Steady-state elimination half-lives of norethindrone and ethinyl estradiol following administration of norethindrone acetate and ethinyl estradiol tablets are approximately 13 hours and 19 hours, respectively.

Special Population

Race:

The effect of race on the disposition of Tilia Fe has not been evaluated.

Renal Insufficiency

The effect of renal disease on the disposition of Tilia Fe has not been evaluated. In premenopausal women with chronic renal failure undergoing peritoneal dialysis who received multiple doses of an oral contraceptive containing ethinyl estradiol and norethindrone, plasma ethinyl estradiol concentrations were higher and norethindrone concentrations were unchanged compared to concentrations in premenopausal women with normal renal function.

Hepatic Insufficiency

The effect of hepatic disease on the disposition of Tilia Fe has not been evaluated. However, ethinyl estradiol and norethindrone may be poorly metabolized in patients with impaired liver function.

Drug-Drug Interactions

Numerous drug-drug interactions have been reported for oral contraceptives. A summary of these is found under PRECAUTIONS, Drug Interactions.

INDICATIONS AND USAGE

Tilia Fe is indicated for the prevention of pregnancy in women who elect to use oral contraceptives as a method of contraception.

Tilia Fe is indicated for the treatment of moderate acne vulgaris in females, ≥15 years of age, who have no known contraindications to oral contraceptive therapy, desire oral contraception, have achieved menarche, and are unresponsive to topical anti-acne medications.

Tilia Fe should be used for the treatment of acne only if the patient desires an oral contraceptive for birth control and plans to stay on it for at least 6 months.

Oral contraceptives are highly effective for pregnancy prevention. Table 2 lists the typical accidental pregnancy rates for users of combination oral contraceptives and other methods of contraception. The efficacy of these contraceptive methods, except sterilization, depends upon the reliability with which they are used. Correct and consistent use of methods can result in lower failure rates.

Table 2. Percentage of Women Experiencing an Unintended Pregnancy During the First Year of Typical Use and the First Year of Perfect Use of Contraception and the Percentage Continuing Use at the End of the First Year. United States.

 |  | % of Women Experiencing an Unintended Pregnancy within the First Year of Use |  | % of Women Continuing Use at One Year^3
Method |  | Typical Use^1 | Perfect Use^2
(1) |  | (2) | (3) | (4)
Chance^4 |  | 85 | 85
Spermicides^5 |  | 26 | 6 | 40
Periodic Abstinence |  | 25 |  | 63
 | Calendar |  | 9
 | Ovulation Method |  | 3
 | Symptothermal^6 |  | 2
 | Post-ovulation |  | 1
Cap^7
 | Parous Women | 40 | 26 | 42
 | Nulliparous Women | 20 | 9 | 56
Sponge
 | Parous Women | 40 | 20 | 42
 | Nulliparous Women | 20 | 9 | 56
Diaphragm^7 |  | 20 | 6 | 56
Withdrawal |  | 19 | 4
Condom^8
 | Female (Reality) | 21 | 5 | 56
 | Male | 14 | 3 | 61
Pill |  | 5 |  | 71
 | Progestin only |  | 0.5
 | Combined |  | 0.1
IUD
 | Progesterone T | 2.0 | 1.5 | 81
 | Copper T380A | 0.8 | 0.6 | 78
 | LNg 20 | 0.1 | 0.1 | 81
Depo-Provera® |  | 0.3 | 0.3 | 70
Norplant® and Norplant-2® |  | 0.05 | 0.05 | 88
Female Sterilization |  | 0.5 | 0.5 | 100
Male Sterilization |  | 0.15 | 0.10 | 100
Emergency Contraceptives Pills: Treatment initiated within 72 hours after unprotected intercourse reduces the risk of pregnancy by at least 75%^9.
Lactational Amenorrhea Method: LAM is a highly effective, temporary method of contraception. ^10
Source: Trussell J, The Essentials of Contraception. In Hatcher RA, Trussell J, Stewart F, Cates W, Stewart GK, Kowel D, Guest F, Contraceptive Technology: Seventeenth Revised Edition. New York NY: Irvington Publishers, 1998.

^1 Among typical couples who initiate use of a method (not necessarily for the first time), the

percentage who experience an accidental pregnancy during the first year if they do not stop use

for any other reason.

^2 Among couples who initiate use of a method (not necessarily for the first time) and who use it

perfectly (both consistently and correctly), the percentage who experience an accidental

pregnancy during the first year if they do not stop use for any other reason.

^3 Among couples attempting to avoid pregnancy, the percentage who continue to use a method

for 1 year.

^4 The percentages becoming pregnant in columns (2) and (3) are based on data from populations

where contraception is not used and from women who cease using contraception in order to

become pregnant. Among such populations, about 89% become pregnant within one year. This

estimate was lowered slightly (to 85%) to represent the percent who would become pregnant

within one year among women now relying on reversible methods of contraception if they

abandoned contraception altogether.

^5 Foams, creams, gels, vaginal suppositories, and vaginal film.

^6 Cervical mucus (ovulation) method supplemented by calendar in the pre-ovulatory and basal

body temperature in the post-ovulatory phases.

^7 With spermicidal cream or jelly.

^8 Without spermicides.

^9 The treatment schedule is one dose within 72 hours after unprotected intercourse, and a second

dose 12 hours after the first dose. The Food and Drug Administration has declared the following

brands of oral contraceptives to be safe and effective for emergency contraception: Ovral® (1

dose is 2 white pills), Alesse® (1 dose is 5 pink pills), Nordette® or Levlen® (1 dose is 4 lightorange

pills), Lo/Ovral® (1 dose is 4 white pills), Triphasil® or Tri-Levlen® (1 dose is 4 yellow

pills).

^10 However, to maintain effective protection against pregnancy, another method of contraception

must be used as soon as menstruation resumes, the frequency or duration of breastfeeds is

reduced, bottle feeds are introduced, or the baby reaches 6 months of age.

Norethindrone acetate and ethinyl estradiol tablets were evaluated for the treatment of acne vulgaris in two randomized, double-blind, placebo-controlled, multicenter, Phase 3, six (28-day) cycle studies. A total of 296 patients received norethindrone acetate and ethinyl estradiol tablets and 295 received placebo. Mean age at enrollment for both groups was 24 years. At six months each study demonstrated a statistically significant difference between norethindrone acetate and ethinyl estradiol tablets and placebo for mean change from baseline in lesion counts (see Table 3 and Figure 2). Each study also demonstrated overall treatment success in the investigator's global evaluation. Patients with severe androgen excess were not studied.

Table 3. Acne Vulgaris Indication Pooled Data 376-403 and 376-404 Observed Means at Six Months and at Baseline* Intent To Treat Population

 |  | Norethindrone acetate and ethinyl estradiol tablets N = 296 |  | Placebo N = 295 |  | Difference in Counts Between Norethindrone acetate and ethinyl estradiol tablets and Placebo at Six Months (95% CI)†
Number of Lesions |  | Counts | % reduction | Counts | % reduction
INFLAMMATORY LESIONS
 | Baseline Mean | 29 |  | 29
 | Six Month Mean | 14 | 52% | 17 | 41% | 33 ±2
NON-INFLAMMATORY LESIONS
 | Baseline Mean | 44 |  | 43
 | Six Month Mean | 27 | 38% | 32 | 25% | 5 ±3.5
TOTAL LESIONS
 | Baseline Mean | 74 |  | 72
 | Six Month Mean | 42 | 43% | 49 | 32% | 7 ±5

*Numbers rounded to nearest integer

† Limits for 95% Confidence Interval; not adjusted for baseline differences

Norethindrone acetate and ethinyl estradiol tablet users who started with about 74 acne lesions had about 42 lesions after 6 months of treatment. Placebo users who started with about 72 acne lesions had about 49 lesions after the same duration of treatment.

CONTRAINDICATIONS

Oral contraceptives should not be used in women who currently have the following:

• Thrombophlebitis or thromboembolic disorders

• A past history of deep vein thrombophlebitis or thromboembolic disorders

• Cerebral vascular or coronary artery disease

• Known or suspected carcinoma of the breast

• Carcinoma of the endometrium or other known or suspected estrogen-dependent neoplasia

• Undiagnosed abnormal genital bleeding

• Cholestatic jaundice of pregnancy or jaundice with prior pill use

• Hepatic adenomas or carcinomas

• Known or suspected pregnancy

• Are receiving Hepatitis C drug combinations containing ombitasvir/paritaprevir/ritonavir, with or without dasabuvir, due to the potential for ALT elevations (see Warnings, RISK OF LIVER ENZYME ELEVATIONS WITH CONCOMITANT HEPATITIS C TREATMENT).

WARNINGS

BOXED WARNING

Cigarette smoking increases the risk of serious cardiovascular side effects from oral contraceptive use. This risk increases with age and with heavy smoking (15 or more cigarettes per day) and is quite marked in women over 35 years of age. Women who use oral contraceptives should be strongly advised not to smoke.

The use of oral contraceptives is associated with increased risks of several serious conditions including myocardial infarction, thromboembolism, stroke, hepatic neoplasia, and gallbladder disease, although the risk of serious morbidity or mortality is very small in healthy women without underlying risk factors. The risk of morbidity and mortality increases significantly in the presence of other underlying risk factors such as hypertension, hyperlipidemias, obesity, and diabetes.

Practitioners prescribing oral contraceptives should be familiar with the following information relating to these risks.

The information contained in this package insert is principally based on studies carried out in patients who used oral contraceptives with higher formulations of estrogens and progestogens than those in common use today. The effect of long-term use of the oral contraceptives with lower formulations of both estrogens and progestogens remains to be determined.

Throughout this labeling, epidemiological studies reported are of two types: retrospective or case control studies and prospective or cohort studies. Case control studies provide a measure of the relative risk of a disease, namely, a ratio of the incidence of a disease among oral contraceptive users to that among nonusers. The relative risk does not provide information on the actual clinical occurrence of a disease.

Cohort studies provide a measure of attributable risk, which is the difference in the incidence of disease between oral contraceptive users and nonusers. The attributable risk does provide information about the actual occurrence of a disease in the population (adapted from References 8 and 9 with the author's permission). For further information, the reader is referred to a text on epidemiological methods.

1. Thromboembolic Disorders and Other Vascular Problems

a. Myocardial infarction

An increased risk of myocardial infarction has been attributed to oral contraceptive use. This risk is primarily in smokers or women with other underlying risk factors for coronary artery disease such as hypertension, hypercholesterolemia, morbid obesity, and diabetes. The relative risk of heart attack for current oral contraceptive users has been estimated to be two to six. The risk is very low under the age of 30.

Smoking in combination with oral contraceptive use has been shown to contribute substantially to the incidence of myocardial infarctions in women in their mid-thirties or older with smoking accounting for the majority of excess cases. Mortality rates associated with circulatory disease have been shown to increase substantially in smokers over the age of 35 and non-smokers over the age of 40 (Figure 3) among women who use oral contraceptives.

Oral contraceptives may compound the effects of well-known risk factors, such as hypertension, diabetes, hyperlipidemias, age and obesity. In particular, some progestogens are known to decrease HDL cholesterol and cause glucose intolerance, while estrogens may create a state of hyperinsulinism. Oral contraceptives have been shown to increase blood pressure among users (see Section 10 in WARNINGS). Similar effects on risk factors have been associated with an increased risk of heart disease. Oral contraceptives must be used with caution in women with cardiovascular disease risk factors.

b. Thromboembolism

An increased risk of thromboembolic and thrombotic disease associated with the use of oral contraceptives is well established. Case control studies have found the relative risk of users compared to nonusers to be 3 for the first episode of superficial venous thrombosis, 4 to 11 for deep vein thrombosis or pulmonary embolism, and 1.5 to 6 for women with predisposing conditions for venous thromboembolic disease. Cohort studies have shown the relative risk to be somewhat lower, about 3 for new cases and about 4.5 for new cases requiring hospitalization. The risk of thromboembolic disease due to oral contraceptives is not related to length of use and disappears after pill use is stopped.

A two- to four-fold increase in relative risk of postoperative thromboembolic complications has been reported with the use of oral contraceptives. The relative risk of venous thrombosis in women who have predisposing conditions is twice that of women without such medical conditions. If feasible, oral contraceptives should be discontinued at least 4 weeks prior to and for 2 weeks after elective surgery of a type associated with an increase in risk of thromboembolism and during and following prolonged immobilization. Since the immediate postpartum period is also associated with an increased risk of thromboembolism, oral contraceptives should be started no earlier than 4 to 6 weeks after delivery in women who elect not to breastfeed.

c. Cerebrovascular disease

Oral contraceptives have been shown to increase both the relative and attributable risks of cerebrovascular events (thrombotic and hemorrhagic strokes), although, in general, the risk is greatest among older (>35 years), hypertensive women who also smoke. Hypertension was found to be a risk factor for both users and nonusers, for both types of strokes, while smoking interacted to increase the risk for hemorrhagic strokes.

In a large study, the relative risk of thrombotic strokes has been shown to range from 3 for normotensive users to 14 for users with severe hypertension. The relative risk of hemorrhagic stroke is reported to be 1.2 for non-smokers who used oral contraceptives, 2.6 for smokers who did not use oral contraceptives, 7.6 for smokers who used oral contraceptives, 1.8 for normotensive users, and 25.7 for users with severe hypertension. The attributable risk is also greater in older women.

d. Dose-related risk of vascular disease from oral contraceptives

A positive association has been observed between the amount of estrogen and progestogen in oral contraceptives and the risk of vascular disease. A decline in serum high-density lipoproteins (HDL) has been reported with many progestational agents. A decline in serum high-density lipoproteins has been associated with an increased incidence of ischemic heart disease. Because estrogens increase HDL cholesterol, the net effect of an oral contraceptive depends on a balance achieved between doses of estrogen and progestin and the nature of the progestin used in the contraceptives. The amount and activity of both hormones should be considered in the choice of an oral contraceptive.

Minimizing exposure to estrogen and progestogen is in keeping with good principles of therapeutics. For any particular oral contraceptive, the dosage regimen prescribed should be one which contains the least amount of estrogen and progestogen that is compatible with the needs of the individual patient. New acceptors of oral contraceptive agents should be started on preparations containing the lowest dose of estrogen which produces satisfactory results for the patient.

e. Persistence of risk of vascular disease

There are two studies which have shown persistence of risk of vascular disease for ever-users of oral contraceptives. In a study in the United States, the risk of developing myocardial infarction after discontinuing oral contraceptives persists for at least 9 years for women 40-49 years who had used oral contraceptives for 5 or more years, but this increased risk was not demonstrated in other age groups. In another study in Great Britain, the risk of developing cerebrovascular disease persisted for at least 6 years after discontinuation of oral contraceptives, although excess risk was very small. However, both studies were performed with oral contraceptive formulations containing 50 mcg or higher of estrogens.

2. Estimates of Mortality from Contraceptive Use

One study gathered data from a variety of sources which have estimated the mortality rate associated with different methods of contraception at different ages (Table 4). These estimates include the combined risk of death associated with contraceptive methods plus the risk attributable to pregnancy in the event of method failure. Each method of contraception has its specific benefits and risks. The study concluded that with the exception of oral contraceptive users 35 and older who smoke and 40 and older who do not smoke, mortality associated with all methods of birth control is low and below that associated with childbirth. The observation of a possible increase in risk of mortality with age for oral contraceptive users is based on data gathered in the 1970's but not reported until 1983. However, current clinical practice involves the use of lower estrogen dose formulations combined with careful restriction of oral contraceptive use to women who do not have the various risk factors listed in this labeling.

Because of these changes in practice and, also, because of some limited new data which suggest that the risk of cardiovascular disease with the use of oral contraceptives may now be less than previously observed (Porter JB, Hunter J, Jick H, et al. Oral contraceptives and nonfatal vascular disease. Obstet Gynecol 1985;66:1-4; and Porter JB, Hershel J, Walker AM. Mortality among oral contraceptive users. Obstet Gynecol 1987;70:29-32), the Fertility and Maternal Health Drugs Advisory Committee was asked to review the topic in 1989. The Committee concluded that although cardiovascular disease risks may be increased with oral contraceptive use after age 40 in healthy nonsmoking women (even with the newer low-dose formulations), there are greater potential health risks associated with pregnancy in older women and with the alternative surgical and medical procedures which may be necessary if such women do not have access to effective and acceptable means of contraception.

Therefore, the Committee recommended that the benefits of oral contraceptive use by healthy non-smoking women over 40 may outweigh the possible risks. Of course, older women, as all women who take oral contraceptives, should take the lowest possible dose formulation that is effective.

3. Carcinoma of the Reproductive Organs and Breasts

Epidemiologic studies have been conducted examining the relationship between combination oral contraceptives and breast cancer. Norethindrone and ethinyl estradiol tablets were not included in these studies, and the majority of the combination oral contraceptives used by women in these studies have higher doses of estrogen than norethindrone and ethinyl estradiol tablets. These studies suggest that the risk of having breast cancer diagnosed may be slightly increased among current and recent users of combination oral contraceptives; however, these studies do not provide evidence for causation. The observed pattern of increased risk of breast cancer diagnosis may be due to earlier detection of breast cancer in combination oral contraceptive users, the biological effects of combination oral contraceptives, or a combination of reasons. The risk appears to decrease over time after combination oral contraceptive discontinuation, and by 10 years after cessation of combination oral contraceptive use, the additional risk disappears. The risk does not appear to increase with duration of use and no consistent relationships have been found with age at first use or doses studied or type of steroid. Most studies show a similar pattern of risk with combination oral contraceptive use regardless of a woman's reproductive history or her family breast cancer history. Breast cancers diagnosed in current or previous combination oral contraceptive users tend to be less clinically advanced than in nonusers.

Women who currently have or have had breast cancer should not use oral contraceptives because breast cancer is a hormonally-sensitive tumor.

Some studies suggest that oral contraceptive use has been associated with an increase in the risk of cervical intraepithelial neoplasia in some populations of women. However, there continues to be controversy about the extent to which such findings may be due to differences in sexual behavior and other factors.

4. Hepatic Neoplasia

Benign hepatic adenomas are associated with oral contraceptive use, although the incidence of benign tumors is rare in the United States. Indirect calculations have estimated the attributable risk to be in the range of 3.3 cases/ 1 00,000 for users, a risk that increases after 4 or more years of use. Rupture of rare, benign, hepatic adenomas may cause death through intra-abdominal hemorrhage.

Studies from Britain have shown an increased risk of developing hepatocellular carcinoma in long-term (>8years) oral contraceptive users. However, these cancers are extremely rare in the US, and the attributable risk (the excess incidence) of liver cancers in oral contraceptive users approaches less than one per million users.

5. Risk of Liver Enzyme Elevations with Concomitant Hepatitis C Treatment

During clinical trials with the Hepatitis C combination drug regimen that contains ombitasvir/paritaprevir/ritonavir, with or without dasabuvir, ALT elevations greater than 5 times the upper limit of normal (ULN), including some cases greater than 20 times the ULN, were significantly more frequent in women using ethinyl estradiol-containing medications such as COCs. Discontinue Tilia Fe prior to starting therapy with the combination drug regimen ombitasvir/paritaprevir/ritonavir, with or without dasabuvir (see Contraindications). Tilia Fe can be restarted approximately 2 weeks following completion of treatment with the combination drug regimen.

6. Ocular Lesions

There have been clinical case reports of retinal thrombosis associated with the use of oral contraceptives. Oral contraceptives should be discontinued if there is unexplained partial or complete loss of vision; onset of proptosis or diplopia; papilledema; or retinal vascular lesions. Appropriate diagnostic and therapeutic measures should be undertaken immediately.

7. Oral Contraceptive Use Before and During Early Pregnancy

Extensive epidemiological studies have revealed no increased risk of birth defects in women who have used oral contraceptives prior to pregnancy. Studies also do not suggest a teratogenic effect, particularly insofar as cardiac anomalies and limb reduction defects are concerned, when taken inadvertently during early pregnancy.

The administration of oral contraceptives to induce withdrawal bleeding should not be used as a test for pregnancy. Oral contraceptives should not be used during pregnancy to treat threatened or habitual abortion.

It is recommended that for any patient who has missed two consecutive periods, pregnancy should be ruled out before continuing oral contraceptive use. If the patient has not adhered to the prescribed schedule, the possibility of pregnancy should be considered at the time of the first missed period. Oral contraceptive use should be discontinued if pregnancy is confirmed.

8. Gallbladder Disease

Earlier studies have reported an increased lifetime relative risk of gallbladder surgery in users of oral contraceptives and estrogens. More recent studies, however, have shown that the relative risk of developing gallbladder disease among oral contraceptive users may be minimal. The recent findings of minimal risk may be related to the use of oral contraceptive formulations containing lower hormonal doses of estrogens and progestogens.

9. Carbohydrate and Lipid Metabolic Effects

Oral contraceptives have been shown to cause glucose intolerance in a significant percentage of users. Oral contraceptives containing greater than 75 mcg of estrogens cause hyperinsulinism, while lower doses of estrogen cause less glucose intolerance. Progestogens increase insulin secretion and create insulin resistance, this effect varying with different progestational agents. However, in the non-diabetic woman, oral contraceptives appear to have no effect on fasting blood glucose. Because of these demonstrated effects, prediabetic and diabetic women should be carefully observed while taking oral contraceptives.

A small proportion of women will have persistent hypertriglyceridemia while on the pill. As discussed earlier (see WARNINGS 1 a. and 1 d.), changes in serum triglycerides and lipoprotein levels have been reported in oral contraceptive users.

10. Elevated Blood Pressure

An increase in blood pressure has been reported in women taking oral contraceptives and this increase is more likely in older oral contraceptive users and with continued use. Data from the Royal College of General Practitioners and subsequent randomized trials have shown that the incidence of hypertension increases with increasing concentrations of progestogens.

Women with a history of hypertension or hypertension-related diseases or renal disease should be encouraged to use another method of contraception. If women elect to use oral contraceptives, they should be monitored closely, and if significant elevation of blood pressure occurs, oral contraceptives should be discontinued. For most women, elevated blood pressure will return to normal after stopping oral contraceptives, and there is no difference in the occurrence of hypertension among ever and never users.

11. Headache

The onset or exacerbation of migraine or development of headache with a new pattern which is recurrent, persistent, or severe requires discontinuation of oral contraceptives and evaluation of the cause.

12. Bleeding Irregularities

Breakthrough bleeding and spotting are sometimes encountered in patients on oral contraceptives, especially during the first three months of use. Non-hormonal causes should be considered, and adequate diagnostic measures taken to rule out malignancy or pregnancy in the event of prolonged breakthrough bleeding, as in the case of any abnormal vaginal bleeding. If pathology has been excluded, time or a change to another formulation may solve the problem. In the event of amenorrhea, pregnancy should be ruled out.

Some women may encounter post-pill amenorrhea or oligomenorrhea, especially when such a condition was preexistent.

PRECAUTIONS

2. Physical Examination and Follow-Up

It is good medical practice for all women to have annual history and physical examinations, including women using oral contraceptives. The physical examination, however, may be deferred until after initiation of oral contraceptives if requested by the woman and judged appropriate by the clinician. The physical examination should include special reference to blood pressure, breasts, abdomen and pelvic organs, including cervical cytology, and relevant laboratory tests. In case of undiagnosed, persistent or recurrent abnormal vaginal bleeding, appropriate measures should be conducted to rule out malignancy. Women with a strong family history of breast cancer or who have breast nodules should be monitored with particular care.

3. Lipid Disorders

Women who are being treated for hyperlipidemia should be followed closely if they elect to use oral contraceptives. Some progestogens may elevate LDL levels and may render the control of hyperlipidemias more difficult.

4. Liver Function

If jaundice develops in any woman receiving such drugs, the medication should be discontinued. Steroid hormones may be poorly metabolized in patients with impaired liver function.

5. Fluid Retention

Oral contraceptives may cause some degree of fluid retention. They should be prescribed with caution, and only with careful monitoring, in patients with conditions which might be aggravated by fluid retention.

6. Emotional Disorders

Women with a history of depression should be carefully observed and the drug discontinued if depression recurs to a serious degree.

7. Contact Lenses

Contact lens wearers who develop visual changes or changes in lens tolerance should be assessed by an ophthalmologist.

8. Drug Interactions

Effects of Other Drugs on Oral Contraceptives

Rifampin: Metabolism of both norethindrone and ethinyl estradiol is increased by rifampin. A reduction in contraceptive effectiveness and increased incidence of breakthrough bleeding and menstrual irregularities have been associated with concomitant use of rifampin.

Anticonvulsants: Anticonvulsants such as phenobarbital, phenytoin, and carbamazepine, have been shown to increase the metabolism of ethinyl estradiol and/or norethindrone, which could result in a reduction in contraceptive effectiveness.

Antibiotics: Pregnancy while taking oral contraceptives has been reported when the oral contraceptives were administered with antimicrobials such as ampicillin, tetracycline, and griseofulvin. However, clinical pharmacokinetic studies have not demonstrated any consistent effect of antibiotics (other than rifampin) on plasma concentrations of synthetic steroids.

Atorvastatin: Coadministration of atorvastatin and an oral contraceptive increased AUC values for norethindrone and ethinyl estradiol by approximately 30% and 20%, respectively.

St. John's Wort: Herbal products containing St. John's Wort (hypericum perforatum) may induce hepatic enzymes (cytochrome P450) and p-glycoprotein transporter and may reduce the effectiveness of oral contraceptives. This may also result in breakthrough bleeding.

Concomitant Use with HCV Combination Therapy – Liver Enzyme Elevation: Do not coadminister Tilia Fe with HCV drug combinations containing ombitasvir/paritaprevir/ritonavir, with or without dasabuvir, due to potential for ALT elevations (see Warnings, RISK OF LIVER ENZYME ELEVATIONS WITH CONCOMITANT HEPATITIS C TREATMENT).

Other: Ascorbic acid and acetaminophen may increase plasma ethinyl estradiol concentrations, possibly by inhibition of conjugation. A reduction in contraceptive effectiveness and increased incidence of breakthrough bleeding has been suggested with phenylbutazone.

Effects of Oral Contraceptives on Other Drugs

Oral contraceptive combinations containing ethinyl estradiol may inhibit the metabolism of other compounds. Increased plasma concentrations of cyclosporine, prednisolone, and theophylline have been reported with concomitant administration of oral contraceptives. In addition, oral contraceptives may induce the conjugation of other compounds. Decreased plasma concentrations of acetaminophen and increased clearance of temazepam, salicylic acid, morphine, and clofibric acid have been noted when these drugs were administered with oral contraceptives.

9. Interactions with Laboratory Tests

Certain endocrine and liver function tests and blood components may be affected by oral contraceptives:

a. Increased prothrombin and factors VII, VIII, IX, and X; decreased antithrombin 3; increased norepinephrine-induced platelet aggregability.

b. Increased thyroid binding globulin (TBG) leading to increased circulating total thyroid hormone, as measured by protein-bound iodine (PBI), T4 by column or by radioimmunoassay. Free T3 resin uptake is decreased, reflecting the elevated TBG; free T4 concentration is unaltered.

c. Other binding proteins may be elevated in serum.

d. Sex-binding globulins are increased and result in elevated levels of total circulating sex steroids and corticoids; however, free or biologically active levels remain unchanged.

e. Triglycerides may be increased.

f. Glucose tolerance may be decreased.

g. Serum folate levels may be depressed by oral contraceptive therapy. This may be of clinical significance if a woman becomes pregnant shortly after discontinuing oral contraceptives.

10. Carcinogenesis

See WARNINGS section.

11. Pregnancy

Pregnancy Category X. See CONTRAINDICATIONS and WARNINGS sections.

12. Nursing Mothers

Small amounts of oral contraceptive steroids have been identified in the milk of nursing mothers, and a few adverse effects on the child have been reported, including jaundice and breast enlargement. In addition, oral contraceptives given in the postpartum period may interfere with lactation by decreasing the quantity and quality of breast milk. If possible, the nursing mother should be advised not to use oral contraceptives but to use other forms of contraception until she has completely weaned her child.

13. Pediatric Use

Safety and efficacy of norethindrone acetate and ethinyl estradiol tablets have been established in women of reproductive age. Safety and efficacy are expected to be the same for postpubertal adolescents under the age of 16 and for users 16 years and older. Use of this product before menarche is not indicated.

14. Geriatric Use

This product has not been studied in women over 65 years of age and is not indicated in this population.

INFORMATION FOR PATIENTS

See patient labeling printed below.

ADVERSE REACTIONS

• An increased risk of the following serious adverse reactions has been associated with the use of oral contraceptives (see WARNINGS section):

• Thrombophlebitis

• Arterial thromboembolism

• Pulmonary embolism

• Myocardial infarction

• Cerebral hemorrhage

• Cerebral thrombosis

• Hypertension

• Gallbladder disease

• Hepatic adenomas or benign liver tumors

There is evidence of an association between the following conditions and the use of oral contraceptives, although additional confirmatory studies are needed:

• Mesenteric thrombosis

• Retinal thrombosis

The following adverse reactions have been reported in patients receiving oral contraceptives and are believed to be drug-related:

• Nausea

• Vomiting

• Gastrointestinal symptoms (such as abdominal cramps and bloating)

• Breakthrough bleeding

• Spotting

• Change in menstrual flow

• Amenorrhea

• Temporary infertility after discontinuation of treatment

• Edema

• Melasma which may persist

• Breast changes: tenderness, enlargement, secretion

• Change in weight (increase or decrease)

• Change in cervical erosion and secretion

• Diminution in lactation when given immediately postpartum

• Cholestatic jaundice

• Migraine

• Rash (allergic)

• Mental depression

• Reduced tolerance to carbohydrates

• Vaginal candidiasis

• Change in corneal curvature (steepening)

• Intolerance to contact lenses

The following adverse reactions have been reported in users of oral contraceptives and the association has been neither confirmed nor refuted:

• Pre-menstrual syndrome

• Cataracts

• Changes in appetite

• Cystitis-like syndrome

• Headache

• Nervousness

• Dizziness

• Hirsutism

• Loss of scalp hair

• Erythema multiforme

• Erythema nodosum

• Hemorrhagic eruption

• Vaginitis

• Porphyria

• Impaired renal function

• Hemolytic uremic syndrome

• Budd-Chiari syndrome

• Acne

• Changes in libido

• Colitis

OVERDOSAGE

Serious ill effects have not been reported following acute ingestion of large doses of oral contraceptives by young children. Overdosage may cause nausea, and withdrawal bleeding may occur in females.

NON-CONTRACEPTIVE HEALTH BENEFITS

The following non-contraceptive health benefits related to the use of oral contraceptives are supported by epidemiological studies which largely utilized oral contraceptive formulations containing estrogen doses exceeding 0.035 mg of ethinyl estradiol or 0.05 mg of mestranol.

Effects on menses:

• Increased menstrual cycle regularity

• Decreased blood loss and decreased incidence of iron deficiency anemia

• Decreased incidence of dysmenorrhea

Effects related to inhibition of ovulation:

• Decreased incidence of functional ovarian cysts

• Decreased incidence of ectopic pregnancies

Effects from long-term use:

• Decreased incidence of fibroadenomas and fibrocystic disease of the breast

• Decreased incidence of acute pelvic inflammatory disease

• Decreased incidence of endometrial cancer

• Decreased incidence of ovarian cancer

DOSAGE AND ADMINISTRATION

The tablet dispenser has been designed to make oral contraceptive dosing as easy and as convenient as possible. The tablets are arranged in four rows of seven tablets each, with the days of the week appearing on the tablet dispenser above the first row of tablets.

Note: Each tablet dispenser has been preprinted with the days of the week, starting with Sunday, to facilitate a Sunday-Start regimen. Six different day label stickers have been provided with the Detailed

Patient & Brief Summary Patient Package Insert in order to accommodate a Day-1 Start regimen. If the patient is using the Day-1 Start regimen, she should place the self-adhesive day label sticker that corresponds to her starting day over the preprinted days.

Important: The patient should be instructed to use an additional method of protection until after the first week of administration in the initial cycle when utilizing the Sunday-Start regimen.

The possibility of ovulation and conception prior to initiation of use should be considered.

Dosage and Administration for 28-Day Dosage Regimen

To achieve maximum contraceptive effectiveness, Tilia Fe should be taken exactly as directed and at intervals not exceeding 24 hours.

Tilia Fe provides a continuous administration regimen consisting of 21 active tablets (pale yellow, light yellow and light brown) and seven brown non-hormone containing tablets of ferrous fumarate. The ferrous fumarate tablets are present to facilitate ease of drug administration via a 28-day regimen and do not serve any therapeutic purpose. There is no need for the patient to count days between cycles because there are no "off-tablet days."

A. Sunday-Start Regimen: The patient begins taking the first pale yellow tablet from the top row of the dispenser (labeled Sunday) on the first Sunday after menstrual flow begins. When menstrual flow begins on Sunday, the first pale yellow is taken on the same day. The patient takes one active tablet daily for 21 days. The last light brown tablet in the dispenser will be taken on a Saturday. Upon completion of all 21 active tablets, and without interruption, the patient takes one brown tablet daily for 7 days. Upon completion of this first course of tablets, the patient begins a second course of 28-day tablets, without interruption, the next day (Sunday), starting with the Sunday active tablet in the top row. Adhering to this regimen of one active tablet daily for 21 days, followed without interruption by one brown tablet daily for 7 days, the patient will start all subsequent cycles on a Sunday.

B. Day-1 Start Regimen: The first day of menstrual flow is Day 1. The patient places the self-adhesive day label sticker that corresponds to her starting day over the preprinted days on the tablet dispenser. She starts taking one active tablet daily, beginning with the first active tablet in the top row. After the last active tablet (at the end of the third row) has been taken, the patient will then take the brown tablets for a week (7 days). For all subsequent cycles, the patient begins a new 28 tablet regimen on the eighth day after taking her last active tablet, again starting with the first tablet in the top row after placing the appropriate day label sticker over the preprinted days on the tablet dispenser. Following this regimen of 21 active tablets and 7 brown tablets, the patient will start all subsequent cycles on the same day of the week as the first course.

Tablets should be taken regularly at the same time each day and can be taken without regard to meals. It should be stressed that efficacy of medication depends on strict adherence to the dosage schedule.

Special Notes on Administration

Menstruation usually begins two or three days, but may begin as late as the fourth or fifth day, after the brown tablets have been started. In any event, the next course of tablets should be started without interruption. If spotting occurs while the patient is taking active tablets, continue medication without interruption.

If the patient forgets to take one or more active tablets, the following is suggested:

One tablet is missed

• take tablet as soon as remembered

• take next tablet at the regular time

Two consecutive tablets are missed (Week 1 or Week 2)

• take two tablets as soon as remembered

• take two tablets the next day

• use another birth control method for seven days following the missed tablets

Two consecutive tablets are missed (Week 3)

Sunday-Start Regimen:

• take one tablet daily until Sunday

• discard remaining tablets

• start new pack of tablets immediately (Sunday)

• use another birth control method for seven days following the missed tablets

Day-1 Start Regimen:

• discard remaining tablets

• start new pack of tablets that same day

• use another birth control method for seven days following the missed tablets

Three (or more) consecutive tablets are missed

Sunday-Start Regimen:

• take one tablet daily until Sunday

• discard remaining tablets

• start new pack of tablets immediately (Sunday)

• use another birth control method for seven days following the missed tablets

Day-1 Start Regimen:

• discard remaining tablets

• start new pack of tablets that same day

• use another birth control method for seven days following the missed tablets

The possibility of ovulation occurring increases with each successive day that scheduled active tablets are missed. While there is little likelihood of ovulation occurring if only one "active" tablet is missed, the possibility of spotting or bleeding is increased. This is particularly likely to occur if two or more consecutive "active" tablets are missed.

If the patient forgets to take any of the seven brown tablets in week four, those brown tablets that were missed are discarded and one brown tablet is taken each day until the pack is empty. A back-up birth control method is not required during this time. A new pack of tablets should be started no later than the eighth day after the last active tablet was taken.

In the rare case of bleeding which resembles menstruation, the patient should be advised to discontinue medication and then begin taking tablets from a new tablet dispenser on the next Sunday or the first day (Day 1) depending on her regimen. Persistent bleeding which is not controlled by this method indicates the need for reexamination of the patient, at which time nonfunctional causes should be considered.

Use of Oral Contraceptives in the Event of a Missed Menstrual Period

1. If the patient has not adhered to the prescribed dosage regimen, the possibility of pregnancy should be considered after the first missed period and oral contraceptives should be withheld until pregnancy has been ruled out.

2. If the patient has adhered to the prescribed regimen and misses two consecutive periods, pregnancy should be ruled out before continuing the contraceptive regimen.

After several months on treatment, bleeding may be reduced to a point of virtual absence. This reduced flow may occur as a result of medication, in which event it is not indicative of pregnancy.

Acne

The timing of initiation of dosing with Tilia Fe for acne should follow the guidelines for use of Tilia Fe as an oral contraceptive. Consult the DOSAGE AND ADMINISTRATION section for oral contraceptives.

HOW SUPPLIED

Tilia Fe (Norethindrone Acetate and Ethinyl Estradiol Tablets, USP and Ferrous Fumarate Tablets) contain five pale yellow tablets, seven light yellow tablets, nine light brown tablets and seven brown tablets in a blister card (NDC 51862-896-01) within a plastic dispenser.

Each of the five pale yellow, biconvex, round tablets (debossed with "H2" on one side) contain 1 mg of norethindrone acetate and 20 mcg of ethinyl estradiol. The next seven light yellow, biconvex, round tablets (debossed with "H3" on one side) contain 1 mg of norethindrone acetate and 30 mcg of ethinyl estradiol. The next nine light brown, biconvex, round tablets (debossed with "H4" on one side) contain 1 mg of norethindrone acetate and 35 mcg of ethinyl estradiol. The last seven brown, biconvex, round tablets (debossed with "F" on one side and "N" on the other side) each contains 75 mg ferrous fumarate.

Tilia Fe Tablets are available in the following configurations:

Carton of 1 compact NDC 51862-896-02

Carton of 3 compacts NDC 51862-896-03

Carton of 6 compacts NDC 51862-896-06

Store at 20°C to 25°C (68°F to 77°F). [See USP Controlled Room Temperature]. Protect from light.

Keep this drug and all drugs out of the reach of children.

Rx Only.

REFERENCES AVAILABLE UPON REQUEST

BRIEF SUMMARY PATIENT PACKAGE INSERT

Tilia Fe (like all oral contraceptives) is intended to prevent pregnancy. It does not protect against transmission of HIV (AIDS) and other sexually transmitted diseases.

Oral contraceptives, also known as "birth control pills" or "the pill," are taken to prevent pregnancy and, when taken correctly, have a failure rate of about 1% per year when used without missing any pills. The typical failure rate of large numbers of pill users is less than 3% per year when women who miss pills are included. For most women oral contraceptives are also free of serious or unpleasant side effects. However, forgetting to take pills considerably increases the chances of pregnancy.

Tilia Fe may also be taken to treat moderate acne in females who are at least 15 years of age, have started having menstrual periods, are able to use the pill and want the pill for birth control, plan to stay on the pill for at least 6 months, and have not improved with acne medicines that are put on the skin.

For the majority of women, oral contraceptives can be taken safely. But there are some women who are at high risk of developing certain serious diseases that can be life-threatening or may cause temporary or permanent disability. The risks associated with taking oral contraceptives increase significantly if you:

• Smoke

• Have high blood pressure, diabetes, high cholesterol

• Have or have had clotting disorders, heart attack, stroke, angina pectoris, cancer of the breast or sex organs, jaundice, or malignant or benign liver tumors.

You should not take the pill if you suspect you are pregnant or have unexplained vaginal bleeding.

BOXED WARNING

Cigarette smoking increases the risk of serious cardiovascular side effects from oral contraceptive use. This risk increases with age and with heavy smoking (15 or more cigarettes per day) and is quite marked in women over 35 years of age. Women who use oral contraceptives should be strongly advised not to smoke.

Most side effects of the pill are not serious. The most common side effects are nausea, vomiting, bleeding between menstrual periods, weight gain, breast tenderness, and difficulty wearing contact lenses. These side effects, especially nausea, vomiting, and breakthrough bleeding, may subside within the first three months of use.

The serious side effects of the pill occur very infrequently, especially if you are in good health and are young. However, you should know that the following medical conditions have been associated with or made worse by the pill:

1. Blood clots in the legs (thrombophlebitis), lungs (pulmonary embolism), stoppage or rupture of a blood vessel in the brain (stroke), blockage of blood vessels in the heart (heart attack or angina pectoris), or other organs of the body. As mentioned above, smoking increases the risk of heart attacks and strokes and subsequent serious medical consequences.

2. Liver tumors, which may rupture and cause severe bleeding. A possible but not definite association has been found with the pill and liver cancer. However, liver cancers are extremely rare. The chance of developing liver cancer from using the pill is thus even rarer.

3. High blood pressure, although blood pressure usually returns to normal when the pill is stopped.

The symptoms associated with these serious side effects are discussed in the detailed leaflet given to you with your supply of pills. Notify your doctor or healthcare provider if you notice any unusual physical disturbances while taking the pill. In addition, drugs such as rifampin, as well as some anticonvulsants and some antibiotics, may decrease oral contraceptive effectiveness.

Do not take the pill if you take any Hepatitis C drug combination containing ombitasvir/paritaprevir/ ritonavir, with or without dasabuvir. This may increase levels of the liver enzyme "alanine aminotransferase" (ALT) in the blood.

Breast cancer has been diagnosed slightly more often in women who use the pill than in women of the same age who do not use the pill. This very small increase in the number of breast cancer diagnoses gradually disappears during the 10 years after stopping use of the pill. It is not known whether the increase in breast cancer diagnoses is caused by the pill. You should have regular breast examinations by a healthcare provider and examine your own breasts monthly. Tell your healthcare provider if you have a family history of breast cancer or if you have had breast nodules or an abnormal mammogram. Women who currently have or have had breast cancer should not use oral contraceptives because breast cancer is a hormone-sensitive tumor. ∙

Some studies have found an increase in the incidence of precancerous lesions of the cervix in women who use oral contraceptives. However, this finding may be related to factors other than the use of oral contraceptives.

Taking the pill provides some important non-contraceptive benefits. These include less painful menstruation, less menstrual blood loss and anemia, fewer pelvic infections, and fewer cancers of the ovary and the lining of the uterus.

Be sure to discuss any medical condition you may have with your healthcare provider. Your healthcare provider will take a medical and family history and examine you before prescribing oral contraceptives. The physical examination may be delayed to another time if you request it and your healthcare provider believes that it is a good medical practice to postpone it. You should be reexamined at least once a year while taking oral contraceptives. The Detailed Patient Information leaflet gives you further information which you should read and discuss with your healthcare provider.

Tilia Fe (like all oral contraceptives) is intended to prevent pregnancy. It does not protect against transmission of HIV (AIDS) and other sexually transmitted diseases such as Chlamydia, genital herpes, genital warts, gonorrhea, hepatitis B, and syphilis.

INSTRUCTIONS TO PATIENT

TABLET DISPENSER

The Tilia Fe tablet dispenser has been designed to make oral contraceptive dosing as easy and as convenient as possible. The tablets are arranged in four rows of seven tablets each, with the days of the week appearing above the first row of tablets.

Each pale yellow, biconvex, round tablet debossed with "H2" on one side contains 1 mg norethindrone acetate and 20 mcg ethinyl estradiol.

Each light yellow, biconvex, round tablet debossed with "H3" on one side contains 1 mg norethindrone acetate and 30 mcg ethinyl estradiol.

Each light brown, biconvex, round tablet debossed with "H4" on one side contains 1 mg norethindrone acetate and 35 mcg ethinyl estradiol.

Each brown, biconvex, round tablet debossed with "F" on one side and "N" on the other side contains 75 mg ferrous fumarate and is intended to help you remember to take the tablets correctly. These brown tablets are not intended to have any health benefit.

DIRECTIONS

To remove a tablet, press down on it with your thumb or finger. The tablet will drop through the back of the tablet dispenser. Do not press with your thumbnail, fingernail, or any other sharp object.

HOW TO TAKE THE PILL

IMPORTANT POINTS TO REMEMBER

BEFORE YOU START TAKING YOUR PILLS:

1. BE SURE TO READ THESE DIRECTIONS:

Before you start taking your pills.

Anytime you are not sure what to do.

2. THE RIGHT WAY TO TAKE THE PILL IS TO TAKE ONE PILL EVERY DAY AT THE SAME TIME. If you miss pills you could get pregnant. This includes starting the pack late. The more pills you miss, the more likely you are to get pregnant.

3. MANY WOMEN HAVE SPOTTING OR LIGHT BLEEDING, OR MAY FEEL SICK TO THEIR STOMACH, DURING THE FIRST 1-3 PACKS OF PILLS. If you do have spotting or light bleeding or feel sick to your stomach, do not stop taking the pill. The problem will usually go away. If it doesn't go away, check with your doctor or clinic.

4. MISSING PILLS CAN ALSO CAUSE SPOTTING OR LIGHT BLEEDING, even when you make up these missed pills. On the days you take 2 pills to make up for missed pills, you could also feel a little sick to your stomach.

5. IF YOU HAVE VOMITING OR DIARRHEA, for any reason, or IF YOU TAKE SOME MEDICINES, including some antibiotics, your birth control pills may not work as well. Use a back-up birth control method (such as condoms or spermicide) until you check with your doctor or clinic.

6. IF YOU HAVE TROUBLE REMEMBERING TO TAKE THE PILL, talk to your doctor or clinic about how to make pill-taking easier or about using another method of birth control.

7. IF YOU HAVE ANY QUESTIONS OR ARE UNSURE ABOUT THE INFORMATION IN THIS LEAFLET, call your doctor or clinic.

BEFORE YOU START TAKING YOUR PILLS

1. DECIDE WHAT TIME OF DAY YOU WANT TO TAKE YOUR PILL. It is important to take it at about the same time every day.

2. LOOK AT YOUR PILL PACK.

The pill pack has 21 "active" (with hormones) pills (pale yellow, light yellow and light brown) to take for 3 weeks, followed by 1 week of "reminder" brown pills (without hormones).

3. ALSO FIND:

1) where on the pack to start taking pills,

2) in what order to take the pills (follow the arrows), and

3) the week numbers as shown in the following pictures:

Each Tilia Fe tablet dispenser contains five pale yellow tablets, seven light yellow tablets, nine light brown tablets, and seven brown tablets. These tablets are to be taken in the following order: one pale yellow tablet each day for five days, then one light yellow tablet each day for seven days, followed by one light brown tablet each day for nine days, and then one brown tablet each day for seven days.

Tilia Fe will contain: 21 ACTIVE PILLS for Weeks 1, 2, and 3. Week 4 will contain BROWN PILLS ONLY.

4. BE SURE YOU HAVE READY AT ALL TIMES:

ANOTHER KIND OF BIRTH CONTROL (such as condoms or spermicide) to use as a back-up in case you miss pills.

An EXTRA, FULL PILL PACK.

WHEN TO START THE FIRST PACK OF PILLS

You have a choice of which day to start taking your first pack of pills. Decide with your doctor or clinic which is the best day for you. Pick a time of day which will be easy to remember.

DAY-1 START:

1. Pick the day label sticker that starts with the first day of your period. (This is the day you start bleeding or spotting, even if it is almost midnight when the bleeding begins.)

2. Place this day label sticker on the tablet dispenser over the area that has the days of the week (starting with Sunday) printed on the plastic.

3. Take the first pale yellow pill of the first pack during the first 24 hours of your period.

4. You will not need to use a back-up method of birth control, since you are starting the pill at the beginning of your period.

SUNDAY START:

1. Take the first pale yellow pill of the first pack on the Sunday after your period starts, even if you are still bleeding. If your period begins on Sunday, start the pack that same day.

2. Use another method of birth control as a back-up method if you have sex anytime from the Sunday you start your first pack until the next Sunday (7 days). Condoms or spermicide are good back-up methods of birth control.

WHAT TO DO DURING THE MONTH

1. TAKE ONE PILL AT THE SAME TIME EVERY DAY UNTIL THE PACK IS EMPTY.

Do not skip pills even if you are spotting or bleeding between monthly periods or feel sick to your stomach (nausea).

Do not skip pills even if you do not have sex very often.

2. WHEN YOU FINISH A PACK OR SWITCH YOUR BRAND OF PILLS:

21 pills: Wait 7 days to start the next pack. You will probably have your period during that week. Be sure that no more than 7 days pass between 21-day packs.

28 pills: Start the next pack on the day after your last "reminder" pill. Do not wait any days between packs.

WHAT TO DO IF YOU MISS PILLS

If you MISS 1 "active" pill:

1. Take it as soon as you remember. Take the next pill at your regular time. This means you may take 2 pills in 1 day.

2. You do not need to use a back-up birth control method if you have sex.

If you MISS 2 "active" pills in a row in Week 1 OR Week 2 of your pack:

1. Take 2 pills on the day you remember and 2 pills the next day.

2. Then take 1 pill a day until you finish the pack.

3. You COULD GET PREGNANT if you have sex in the 7 days after you miss pills. You MUST use another birth control method (such as condoms or spermicide) as a back-up method of birth control until you have taken an "active" pill every day for 7 days.

If you MISS 2 "active" pills in a row in THE 3rd WEEK:

1. If you are a Day-1 Starter:

THROW OUT the rest of the pill pack and start a new pack that same day.

If you are a Sunday Starter:

Keep taking 1 pill every day until Sunday. On Sunday, THROW OUT the rest of the pack and start a new pack of pills that same day.

2. You may not have your period this month, but this is expected. However, if you miss your period 2 months in a row, call your doctor or clinic because you might be pregnant.

3. You COULD GET PREGNANT if you have sex in the 7 days after you miss pills. You MUST use another birth control method (such as condoms or spermicide) as a back-up method of birth control until you have taken an "active" pill every day for 7 days.

If you MISS 3 OR MORE "active" pills in a row (during the first 3 weeks):

1. If you are a Day-1 Starter:

THROW OUT the rest of the pill pack and start a new pack that same day.

If you are a Sunday Starter:

Keep taking 1 pill every day until Sunday. On Sunday, THROW OUT the rest of the pack and start a new pack of pills that same day.

2. You may not have your period this month, but this is expected. However, if you miss your period 2 months in a row, call your doctor or clinic because you might be pregnant.

3. You COULD GET PREGNANT if you have sex in the 7 days after you miss pills. You MUST use another birth control method (such as condoms or spermicide) as a back-up method of birth control until you have taken an "active" pill every day for 7 days.

REMINDER

IF YOU FORGET ANY OF THE 7 BROWN "REMINDER" PILLS IN WEEK 4:

THROW AWAY THE PILLS YOU MISSED.

KEEP TAKING 1 PILL EACH DAY UNTIL THE PACK IS EMPTY.

YOU DO NOT NEED A BACK-UP METHOD.

FINALLY, IF YOU ARE STILL NOT SURE WHAT TO DO ABOUT THE PILLS YOU HAVE MISSED:

Use a BACK-UP METHOD anytime you have sex.

KEEP TAKING ONE "ACTIVE" PILL EACH DAY until you can reach your doctor or clinic.

Based on his or her assessment of your medical needs, your doctor or healthcare provider has prescribed

this drug for you. Do not give this drug to anyone else.

Store at 20° to 25°C (68° to 77°F). [See USP Controlled Room Temperature]. Protect from light.

Keep this and all drugs out of the reach of children.

Rx only

DETAILED PATIENT PACKAGE INSERT

Tilia Fe (like all oral contraceptives) is intended to prevent pregnancy. It does not protect against transmission of HIV (AIDS) and other sexually transmitted diseases.

What You Should Know About Oral Contraceptives

Any woman who considers using oral contraceptives (the "birth control pill'' or "the pill'') should understand the benefits and risks of using this form of birth control. This leaflet will give you much of the information you will need to make this decision and will also help you determine if you are at risk of developing any of the serious side effects of the pill. It will tell you how to use the pill properly so that it will be as effective as possible. However, this leaflet is not a replacement for a careful discussion between you and your healthcare provider. You should discuss the information provided in this leaflet with him or her, both when you first start taking the pill and during your revisits. You should also follow your healthcare provider's advice with regard to regular check-ups while you are on the pill.

EFFECTIVENESS OF ORAL CONTRACEPTIVES

Oral contraceptives or "birth control pills'' or "the pill'' are used to prevent pregnancy and are more effective than other nonsurgical methods of birth control. When they are taken correctly, the chance of becoming pregnant is less than 1% (1 pregnancy per 100 women per year of use) when used perfectly, without missing any pills. Typical failure rates are actually 5% per year. The chance of becoming pregnant increases with each missed pill during a menstrual cycle.

In comparison, typical failure rates for other methods of birth control during the first year of use are as follows:

Implant: <1%

Injection: <1%

IUD: <1 to 2%

Diaphragm with spermicides: 20%

Spermicides alone: 26%

Vaginal Sponge: 20 to 40%

Female sterilization: <1%

Male sterilization: <1%

Cervical Cap: 20 to 40%

Condom alone (male): 14%

Condom alone (female): 21%

Periodic abstinence: 25%

Withdrawal: 19%

No method: 85%

Tilia Fe may also be taken to treat moderate acne if all of the following are true:

• Your doctor says it is safe for you to use the pill

• You are at least 15 years old

• You have started having menstrual periods

• You want to use the pill for birth control

• You plan to stay on the pill for at least 6 months

• Your acne has not improved with acne medicines that you put on your skin

Norethindrone acetate and ethinyl estradiol tablet users who started with about 74 acne pimples had about 42 pimples after 6 months of treatment. Placebo users who started with about 72 acne pimples had about 49 pimples after six months of treatment. Use Tilia Fe to treat acne only if you want the pill for birth control and plan to stay on it for at least 6 months.

WHO SHOULD NOT TAKE ORAL CONTRACEPTIVES

BOXED WARNING

Cigarette smoking increases the risk of serious cardiovascular side effects from oral contraceptive use. This risk increases with age and with heavy smoking (15 or more cigarettes per day) and is quite marked in women over 35 years of age. Women who use oral contraceptives should be strongly advised not to smoke.

Some women should not use the pill. For example, you should not use the pill if you are pregnant or think you may be pregnant. You should also not use the pill if you have any of the following:

• A history of heart attack or stroke

• Blood clots in the legs (thrombophlebitis), lungs (pulmonary embolism), or eyes

• A history of blood clots in the deep veins of your legs

• Chest pain (angina pectoris)

• Known or suspected breast cancer or cancer of the lining of the uterus, cervix, or vagina

• Unexplained vaginal bleeding (until a diagnosis is reached by your doctor)

• Yellowing of the whites of the eyes or of the skin (jaundice) during pregnancy or during previous use of the pill

• Liver tumor (benign or cancerous)

• Known or suspected pregnancy

• Are receiving Hepatitis C drug combination containing ombitasvir/paritaprevir/ ritonavir, with or without dasabuvir. This may increase levels of the liver enzyme "alanine aminotransferase" (ALT) in the blood.

Tell your healthcare provider if you have ever had any of these conditions. Your healthcare provider can recommend a safer method of birth control.

OTHER CONSIDERATIONS BEFORE TAKING ORAL CONTRACEPTIVES

Tell your healthcare provider if you have:

• Breast nodules, fibrocystic disease of the breast, an abnormal breast x-ray or mammogram

• Diabetes

• Elevated cholesterol or triglycerides

• High blood pressure

• Migraine or other headaches or epilepsy

• Mental depression

• Gallbladder, heart, or kidney disease

• History of scanty or irregular menstrual periods

Women with any of these conditions should be checked often by their healthcare provider if they choose to use oral contraceptives.

Also, be sure to inform your doctor or healthcare provider if you smoke or are on any medications.

RISKS OF TAKING ORAL CONTRACEPTIVES

1. Risk of Developing Blood Clots

Blood clots and blockage of blood vessels are the most serious side effects of taking oral contraceptives; in particular, a clot in the leg can cause thrombophlebitis, and a clot that travels to the lungs can cause a sudden blocking of the vessel carrying blood to the lungs. Rarely, clots occur in the blood vessels of the eye and may cause blindness, double vision, or impaired vision.

If you take oral contraceptives and need elective surgery, need to stay in bed for a prolonged illness, or have recently delivered a baby, you may be at risk of developing blood clots. You should consult your doctor about stopping oral contraceptives three to four weeks before surgery and not taking oral contraceptives for two weeks after surgery or during bed rest. You should also not take oral contraceptives soon after delivery of a baby. It is advisable to wait for at least four weeks after delivery if you are not breastfeeding. If you are breastfeeding, you should wait until you have weaned your child before using the pill. (See also the section on Breastfeeding in GENERAL PRECAUTIONS.)

2. Heart Attacks and Strokes

Oral contraceptives may increase the tendency to develop strokes (stoppage or rupture of blood vessels in the brain) and angina pectoris and heart attacks (blockage of blood vessels in the heart). Any of these conditions can cause death or disability.

Smoking greatly increases the possibility of suffering heart attacks and strokes. Furthermore, smoking and the use of oral contraceptives greatly increase the chances of developing and dying of heart disease.

3. Gallbladder Disease

Oral contraceptive users probably have a greater risk than nonusers of having gallbladder disease, although this risk may be related to pills containing high doses of estrogens.

4. Liver Tumors

In rare cases, oral contraceptives can cause benign but dangerous liver tumors. These benign liver tumors can rupture and cause fatal internal bleeding. In addition, a possible but not definite association has been found with the pill and liver cancers in two studies, in which a few women who developed these very rare cancers were found to have used oral contraceptives for long periods. However, liver cancers are extremely rare. The chance of developing liver cancer from using the pill is thus even rarer.

5. Cancer of the Reproductive Organs and Breasts

Breast cancer has been diagnosed slightly more often in women who use the pill than in women of the same age who do not use the pill. This very small increase in the number of breast cancer diagnoses gradually disappears during the 10 years after stopping use of the pill. It is not known whether the increase in breast cancer diagnosis is caused by the pill. You should have regular breast examinations by a healthcare provider and examine your own breasts monthly. Tell your healthcare provider if you have a family history of breast cancer or if you have had breast nodules or an abnormal mammogram. Women who currently have or have had breast cancer should not use oral contraceptives because breast cancer is a hormone-sensitive tumor.

Some studies have found an increase in the incidence of precancerous lesions of the cervix in women who use oral contraceptives. However, this finding may be related to factors other than the use of oral

contraceptives.

ESTIMATED RISK OF DEATH FROM A BIRTH CONTROL METHOD OR PREGNANCY

All methods of birth control and pregnancy are associated with a risk of developing certain diseases which may lead to disability or death. An estimate of the number of deaths associated with different methods of birth control and pregnancy has been calculated and is shown in the following table.

In the above table, the risk of death from any birth control method is less than the risk of childbirth, except for oral contraceptive users over the age of 35 who smoke and pill users over the age of 40 even if they do not smoke. It can be seen in the table that for women aged 15 to 39, the risk of death was highest with pregnancy (7 to 26 deaths per 100,000 women, depending on age). Among pill users who do not smoke, the risk of death was always lower than that associated with pregnancy for any age group, although over the age of 40, the risk increases to 32 deaths per 1 00,000 women, compared to 28 associated with pregnancy at that age. However, for pill users who smoke and are over the age of 35, the estimated number of deaths exceeds those for other methods of birth control. If a woman is over the age of 40 and smokes, her estimated risk of death is four times higher (117/100,000 women) than the estimated risk associated with pregnancy (28/100,000 women) in that age group.

The suggestion that women over 40 who don't smoke should not take oral contraceptives is based on information from older higher dose pills and on less selective use of pills than is practiced today. An Advisory Committee of the FDA discussed this issue in 1989 and recommended that the benefits of oral contraceptive use by healthy, non-smoking women over 40 years of age may outweigh the possible risks.

However, all women, especially older women, are cautioned to use the lowest dose pill that is effective.

WARNING SIGNALS

If any of these adverse effects occur while you are taking oral contraceptives, call your doctor immediately:

• Sharp chest pain, coughing of blood, or sudden shortness of breath (indicating a possible clot in the lung)

• Pain in the calf (indicating a possible clot in the leg)

• Crushing chest pain or heaviness in the chest (indicating a possible heart attack)

• Sudden severe headache or vomiting, dizziness or fainting, disturbances of vision or speech, weakness, or numbness in an arm or leg (indicating a possible stroke)

• Sudden partial or complete loss of vision (indicating a possible clot in the eye)

• Breast lumps (indicating possible breast cancer or fibrocystic disease of the breast; ask your doctor or healthcare provider to show you how to examine your breasts)

• Severe pain or tenderness in the stomach area (indicating a possible ruptured liver tumor)

• Difficulty in sleeping, weakness, lack of energy, fatigue, or change in mood (possibly indicating severe depression)

• Jaundice or a yellowing of the skin or eyeballs, accompanied frequently by fever, fatigue, loss of appetite, dark colored urine, or light colored bowel movements (indicating possible liver problems)

SIDE EFFECTS OF ORAL CONTRACEPTIVES

1. Vaginal Bleeding

Irregular vaginal bleeding or spotting may occur while you are taking the pills. Irregular bleeding may vary from slight staining between menstrual periods to breakthrough bleeding which is a flow much like a regular period. Irregular bleeding occurs most often during the first few months of oral contraceptive use, but may also occur after you have been taking the pill for some time. Such bleeding may be temporary and usually does not indicate serious problems. It is important to continue taking your pills on schedule. If the bleeding occurs in more than one cycle or lasts for more than a few days, talk to your doctor or healthcare provider.

2. Contact Lenses

If you wear contact lenses and notice a change in vision or an inability to wear your lenses, contact your doctor or healthcare provider.

3. Fluid Retention

Oral contraceptives may cause edema (fluid retention) with swelling of the fingers or ankles and may raise your blood pressure. If you experience fluid retention, contact your doctor or healthcare provider.

4. Melasma

A spotty darkening of the skin is possible, particularly of the face.

5. Other Side Effects

Other side effects may include change in appetite, headache, nervousness, depression, dizziness, loss of scalp hair, rash, and vaginal infections.

If any of these side effects bother you, call your doctor or healthcare provider.

GENERAL PRECAUTIONS

1. Missed Periods and Use of Oral Contraceptives Before or During Early Pregnancy

There may be times when you may not menstruate regularly after you have completed taking a cycle of pills. If you have taken your pills regularly and miss one menstrual period, continue taking your pills for the next cycle but be sure to inform your healthcare provider before doing so. If you have not taken the pills daily as instructed and missed a menstrual period, or if you missed two consecutive menstrual periods, you may be pregnant. Check with your healthcare provider immediately to determine whether you are pregnant. Do not continue to take oral contraceptives until you are sure you are not pregnant, but continue to use another method of contraception.

There is no conclusive evidence that oral contraceptive use is associated with an increase in birth defects, when taken inadvertently during early pregnancy. Previously, a few studies had reported that oral contraceptives might be associated with birth defects, but these studies have not been confirmed. Nevertheless, oral contraceptives or any other drugs should not be used during pregnancy unless clearly necessary and prescribed by your doctor. You should check with your doctor about risks to your unborn child of any medication taken during pregnancy.

2. While Breastfeeding

If you are breastfeeding, consult your doctor before starting oral contraceptives. Some of the drug will be passed on to the child in the milk. A few adverse effects on the child have been reported, including yellowing of the skin (jaundice) and breast enlargement. In addition, oral contraceptives may decrease the amount and quality of your milk. If possible, do not use oral contraceptives while breastfeeding. You should use another method of contraception since breastfeeding provides only partial protection from becoming pregnant, and this partial protection decreases significantly as you breastfeed for longer periods of time. You should consider starting oral contraceptives only after you have weaned your child completely.

3. Laboratory Tests

If you are scheduled for any laboratory tests, tell your doctor you are taking birth control pills. Certain blood tests may be affected by birth control pills.

4. Drug Interactions

Certain drugs may interact with birth control pills to make them less effective in preventing pregnancy or cause an increase in breakthrough bleeding. Such drugs include rifampin; drugs used for epilepsy such as barbiturates (for example, phenobarbital), carbamazepine, and phenytoin (Dilantin® is one brand of this drug); phenylbutazone; and possibly St. John's Wort and certain antibiotics. You may need to use additional contraception when you take drugs which can make oral contraceptives less effective.

Birth control pills interact with certain drugs. These drugs include acetaminophen, clofibric acid, cyclosporine, morphine, prednisolone, salicylic acid, temazepam, and theophylline. You should tell your doctor if you are taking any of these medications.

5. Sexually Transmitted Diseases

Tilia Fe (like all oral contraceptives) is intended to prevent pregnancy. It does not protect against transmission of HIV (AIDS) and other sexually transmitted diseases such as Chlamydia, genital herpes, genital warts, gonorrhea, hepatitis B, and syphilis.

INSTRUCTIONS TO PATIENT

TABLET DISPENSER

The Tilia Fe tablet dispenser has been designed to make oral contraceptive dosing as easy and as convenient as possible. The tablets are arranged in four rows of seven tablets each, with the days of the week appearing above the first row of tablets.

Each pale yellow, biconvex, round tablet debossed with "H2" on one side contains 1 mg norethindrone acetate and 20 mcg ethinyl estradiol.

Each light yellow, biconvex, round tablet debossed with "H3" on one side contains 1 mg norethindrone acetate and 30 mcg ethinyl estradiol.

Each light brown, biconvex, round tablet debossed with "H4" on one side contains 1 mg norethindrone acetate and 35 mcg ethinyl estradiol.

Each brown, biconvex, round tablet debossed with "F" on one side and "N" on the other side contains 75 mg ferrous fumarate and is intended to help you remember to take the tablets correctly. These brown tablets are not intended to have any health benefit.

DIRECTIONS

To remove a tablet, press down on it with your thumb or finger. The tablet will drop through the back of the tablet dispenser. Do not press with your thumbnail, fingernail, or any other sharp object.

HOW TO TAKE THE PILL

IMPORTANT POINTS TO REMEMBER

BEFORE YOU START TAKING YOUR PILLS:

1. BE SURE TO READ THESE DIRECTIONS:

Before you start taking your pills.

Anytime you are not sure what to do.

2. THE RIGHT WAY TO TAKE THE PILL IS TO TAKE ONE PILL EVERY DAY AT THE SAME TIME. If you miss pills you could get pregnant. This includes starting the pack late. The more pills you miss, the more likely you are to get pregnant.

3. MANY WOMEN HAVE SPOTTING OR LIGHT BLEEDING, OR MAY FEEL SICK TO THEIR STOMACH, DURING THE FIRST 1-3 PACKS OF PILLS. If you do have spotting or light bleeding or feel sick to your stomach, do not stop taking the pill. The problem will usually go away. If it doesn't go away, check with your doctor or clinic.

4. MISSING PILLS CAN ALSO CAUSE SPOTTING OR LIGHT BLEEDING, even when you make up these missed pills. On the days you take 2 pills to make up for missed pills, you could also feel a little sick to your stomach.

5. IF YOU HAVE VOMITING OR DIARRHEA, for any reason, or IF YOU TAKE SOME MEDICINES, including some antibiotics, your birth control pills may not work as well. Use a back-up birth control method (such as condoms or spermicide) until you check with your doctor or clinic.

6. IF YOU HAVE TROUBLE REMEMBERING TO TAKE THE PILL, talk to your doctor or clinic about how to make pill-taking easier or about using another method of birth control.

7. IF YOU HAVE ANY QUESTIONS OR ARE UNSURE ABOUT THE INFORMATION IN THIS LEAFLET, call your doctor or clinic.

BEFORE YOU START TAKING YOUR PILLS

1. DECIDE WHAT TIME OF DAY YOU WANT TO TAKE YOUR PILL. It is important to take it at about the same time every day.

2. LOOK AT YOUR PILL PACK.

The pill pack has 21 "active" pills (with hormones) to take for 3 weeks, followed by 1 week of "reminder" brown pills (without hormones).

3. ALSO FIND:

1) where on the pack to start taking pills,

2) in what order to take the pills (follow the arrows), and

3) the week numbers as shown in the following pictures:

Each Tilia Fe tablet dispenser contains five pale yellow tablets, seven light yellow tablets, nine light brown tablets, and seven brown tablets. These tablets are to be taken in the following order: one pale yellow tablet each day for five days, then one light yellow tablet each day for seven days, followed by one light brown tablet each day for nine days, and then one brown tablet each day for seven days.

Tilia Fe will contain: 21 ACTIVE PILLS for Weeks 1, 2, and 3. Week 4 will contain BROWN PILLS ONLY.

4. BE SURE YOU HAVE READY AT ALL TIMES:

ANOTHER KIND OF BIRTH CONTROL (such as condoms or spermicide) to use as a back-up in case you miss pills.

An EXTRA, FULL PILL PACK.

WHEN TO START THE FIRST PACK OF PILLS

You have a choice of which day to start taking your first pack of pills. Decide with your doctor or clinic which is the best day for you. Pick a time of day which will be easy to remember.

DAY-1 START:

1. Pick the day label sticker that starts with the first day of your period. (This is the day you start bleeding or spotting, even if it is almost midnight when the bleeding begins.)

2. Place this day label sticker on the tablet dispenser over the area that has the days of the week (starting with Sunday) printed on the plastic.

3. Take the first pale yellow pill of the first pack during the first 24 hours of your period.

4. You will not need to use a back-up method of birth control, since you are starting the pill at the beginning of your period.

SUNDAY START:

1. Take the first pale yellow pill of the first pack on the Sunday after your period starts, even if you are still bleeding. If your period begins on Sunday, start the pack that same day.

2. Use another method of birth control as a back-up method if you have sex anytime from the Sunday you start your first pack until the next Sunday (7 days). Condoms or spermicide are good back-up methods of birth control.

WHAT TO DO DURING THE MONTH

1. TAKE ONE PILL AT THE SAME TIME EVERY DAY UNTIL THE PACK IS EMPTY.

Do not skip pills even if you are spotting or bleeding between monthly periods or feel sick to your stomach (nausea).

Do not skip pills even if you do not have sex very often.

2. WHEN YOU FINISH A PACK OR SWITCH YOUR BRAND OF PILLS:

21 pills: Wait 7 days to start the next pack. You will probably have your period during that week. Be sure that no more than 7 days pass between 21-day packs.

28 pills: Start the next pack on the day after your last "reminder" pill. Do not wait any days between packs.

WHAT TO DO IF YOU MISS PILLS

If you MISS 1 "active" pill:

1. Take it as soon as you remember. Take the next pill at your regular time. This means you may take 2 pills in 1 day.

2. You do not need to use a back-up birth control method if you have sex.

If you MISS 2 "active" pills in a row in Week 1 OR Week 2 of your pack:

1. Take 2 pills on the day you remember and 2 pills the next day.

2. Then take 1 pill a day until you finish the pack.

3. You COULD GET PREGNANT if you have sex in the 7 days after you miss pills. You MUST use another birth control method (such as condoms or spermicide) as a back-up method of birth control until you have taken an "active" pill every day for 7 days.

If you MISS 2 "active" pills in a row in THE 3rd WEEK:

1. If you are a Day-1 Starter:

THROW OUT the rest of the pill pack and start a new pack that same day.

If you are a Sunday Starter:

Keep taking 1 pill every day until Sunday. On Sunday, THROW OUT the rest of the pack and start a new pack of pills that same day.

2. You may not have your period this month, but this is expected. However, if you miss your period 2 months in a row, call your doctor or clinic because you might be pregnant.

3. You COULD GET PREGNANT if you have sex in the 7 days after you miss pills. You MUST use another birth control method (such as condoms or spermicide) as a back-up method of birth control until you have taken an "active" pill every day for 7 days.

If you MISS 3 OR MORE "active" pills in a row (during the first 3 weeks):

1. If you are a Day-1 Starter:

THROW OUT the rest of the pill pack and start a new pack that same day.

If you are a Sunday Starter:

Keep taking 1 pill every day until Sunday. On Sunday, THROW OUT the rest of the pack and start a new pack of pills that same day.

2. You may not have your period this month, but this is expected. However, if you miss your period 2 months in a row, call your doctor or clinic because you might be pregnant.

3. You COULD GET PREGNANT if you have sex in the 7 days after you miss pills. You MUST use another birth control method (such as condoms or spermicide) as a back-up method of birth control until you have taken an "active" pill every day for 7 days.

REMINDER:

IF YOU FORGET ANY OF THE 7 BROWN "REMINDER" PILLS IN WEEK 4:

THROW AWAY THE PILLS YOU MISSED.

KEEP TAKING 1 PILL EACH DAY UNTIL THE PACK IS EMPTY.

YOU DO NOT NEED A BACK-UP METHOD.

FINALLY, IF YOU ARE STILL NOT SURE WHAT TO DO ABOUT THE PILLS YOU HAVE MISSED:

Use a BACK-UP METHOD anytime you have sex.

KEEP TAKING ONE "ACTIVE" PILL EACH DAY until you can reach your doctor or clinic.

PREGNANCY DUE TO PILL FAILURE

The incidence of pill failure resulting in pregnancy is approximately 1% (i.e., one pregnancy per 100 women per year) if taken every day as directed, but more typical failure rates are about 5%. If failure does occur, the risk to the fetus is minimal.

PREGNANCY AFTER STOPPING THE PILL

There may be some delay in becoming pregnant after you stop using oral contraceptives, especially if you had irregular menstrual cycles before you used oral contraceptives. It may be advisable to postpone conception until you begin menstruating regularly once you have stopped taking the pill and desire pregnancy.

There does not appear to be any increase in birth defects in newborn babies when pregnancy occurs soon after stopping the pill.

OVERDOSAGE

Serious ill effects have not been reported following ingestion of large doses of oral contraceptives by young children. Overdosage may cause nausea and withdrawal bleeding in females. In case of overdosage, contact your healthcare provider or pharmacist.

OTHER INFORMATION

Your healthcare provider will take a medical and family history and examine you before prescribing oral contraceptives. The physical examination may be delayed to another time if you request it and your healthcare provider believes that it is a good medical practice to postpone it. You should be reexamined at least once a year. Be sure to inform your healthcare provider if there is a family history of any of the conditions listed previously in this leaflet. Be sure to keep all appointments with your healthcare provider, because this is a time to determine if there are early signs of side effects of oral contraceptive use.

Do not use the drug for any condition other than the one for which it was prescribed. This drug has been prescribed specifically for you; do not give it to others who may want birth control pills.

HEALTH BENEFITS FROM ORAL CONTRACEPTIVES

In addition to preventing pregnancy, use of oral contraceptives may provide certain benefits. They are:

• Menstrual cycles may become more regular.

• Blood flow during menstruation may be lighter and less iron may be lost. Therefore, anemia due to iron deficiency is less likely to occur.

• Pain or other symptoms during menstruation may be encountered less frequently.

• Ectopic (tubal) pregnancy may occur less frequently.

• Noncancerous cysts or lumps in the breast may occur less frequently.

• Acute pelvic inflammatory disease may occur less frequently.

• Oral contraceptive use may provide some protection against developing two forms of cancer: cancer of the ovaries and cancer of the lining of the uterus.

If you want more information about birth control pills, ask your doctor or pharmacist. They have a more technical leaflet called the "Physician Insert,'' which you may wish to read.

Remembering to take tablets according to schedule is stressed because of its importance in providing you the greatest degree of protection.

MISSED MENSTRUAL PERIODS

At times there may be no menstrual period after a cycle of pills. Therefore, if you miss one menstrual period but have taken the pills exactly as you were supposed to, continue as usual into the next cycle. If you have not taken the pills correctly and miss a menstrual period, you may be pregnant and should stop taking oral contraceptives until your doctor or healthcare provider determines whether or not you are pregnant. Until you can get to your doctor or healthcare provider, use another form of contraception. If two consecutive menstrual periods are missed, you should stop taking pills until it is determined whether or not you are pregnant. Although there does not appear to be any increase in birth defects in newborn babies, if you become pregnant while using oral contraceptives, you should discuss the situation with your doctor or healthcare provider.

Periodic Examination

Your doctor or healthcare provider will take a complete medical and family history before prescribing oral contraceptives. At that time and about once a year thereafter, he or she will generally examine your blood pressure, breasts, abdomen, and pelvic organs (including a Papanicolaou smear, i.e., test for cancer).

Keep this and all drugs out of the reach of children.

Rx only

Store at 20° to 25°C (68° to 77°F) [See USP Controlled Room Temperature]. Protect from light.

To report SUSPECTED ADVERSE REACTIONS, contact Mayne Pharma Toll-free at 1-844-825-8500 or FDA at 1-800-FDA-1088 or www.fda.gov/medwatch.

Distributed by: Mayne Pharma

Greenville, NC 27834

I 0126 Iss. 07/2020 Rev.A